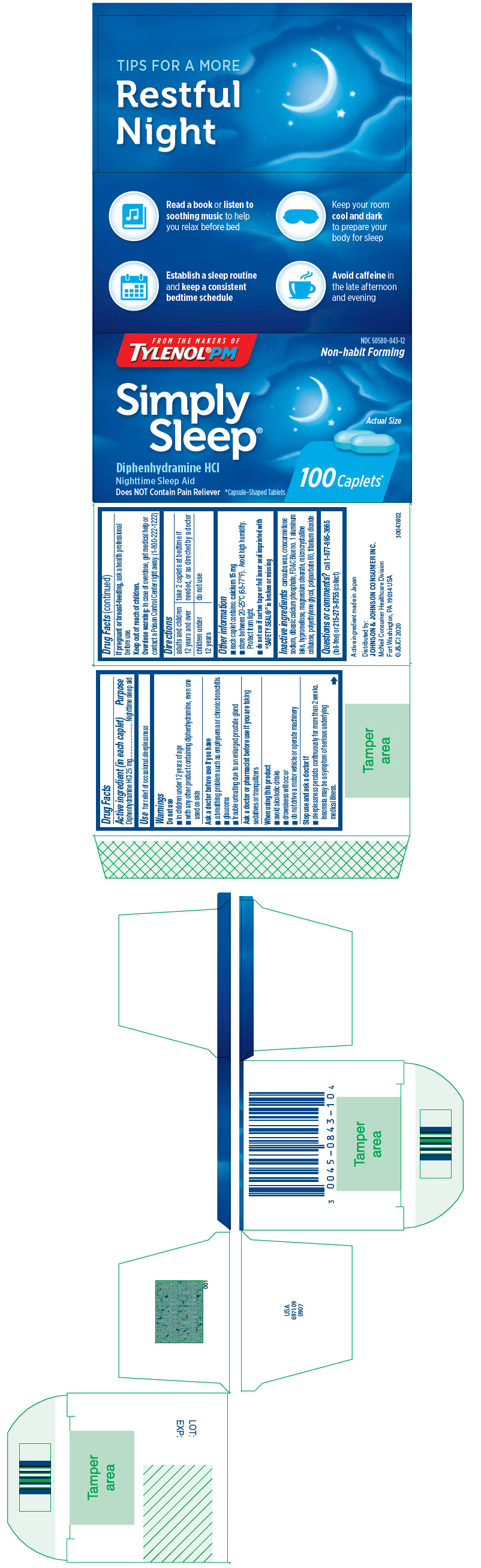 DRUG LABEL: Simply Sleep
NDC: 50580-843 | Form: TABLET, FILM COATED
Manufacturer: Kenvue Brands LLC
Category: otc | Type: HUMAN OTC DRUG LABEL
Date: 20250602

ACTIVE INGREDIENTS: DIPHENHYDRAMINE HYDROCHLORIDE 25 mg/1 1
INACTIVE INGREDIENTS: MICROCRYSTALLINE CELLULOSE; POLYETHYLENE GLYCOL, UNSPECIFIED; POLYSORBATE 80; TITANIUM DIOXIDE; CARNAUBA WAX; CROSCARMELLOSE SODIUM; DIBASIC CALCIUM PHOSPHATE DIHYDRATE; FD&C BLUE NO. 1 ALUMINUM LAKE; HYPROMELLOSE, UNSPECIFIED; MAGNESIUM STEARATE

Simply Sleep

Drug Facts

Active ingredient (in each caplet)

Diphenhydramine HCl 25 mg

Purpose

Nighttime sleep aid

Use

for relief of occasional sleeplessness

Warnings

Do not use

- in children under 12 years of age
- with any other product containing diphenhydramine, even one used on skin

Ask a doctor before use if you have

- a breathing problem such as emphysema or chronic bronchitis
- glaucoma
- trouble urinating due to an enlarged prostate gland

Ask a doctor or pharmacist before use if you are taking sedatives or tranquilizers

When using this product

- avoid alcoholic drinks
- drowsiness will occur
- do not drive a motor vehicle or operate machinery

Stop use and ask a doctor if

- sleeplessness persists continuously for more than 2 weeks. Insomnia may be a symptom of serious underlying medical illness.

PREGNANCY OR BREAST FEEDING

If pregnant or breast-feeding, ask a health professional before use.

Keep out of reach of children.

Overdose warning

In case of overdose, get medical help or contact a Poison Control Center right away. (1-800-222-1222)

Directions

adults and children 12 years and over | take 2 caplets at bedtime if needed, or as directed by a doctor
children under 12 years | do not use

Other information

- each caplet contains: calcium 15 mg
- store between 20-25°C (68-77°F). Avoid high humidity. Protect from light.
- do not use if carton tape or foil inner seal imprinted with "SAFETY SEAL®" is broken or missing

Inactive ingredients

carnauba wax, croscarmellose sodium, dibasic calcium phosphate, FD&C Blue no. 1 aluminum lake, hypromellose, magnesium stearate, microcrystalline cellulose, polyethylene glycol, polysorbate 80, titanium dioxide

Questions or comments?

call 1-877-895-3665 (toll-free) or 215-273-8755 (collect)

PRINCIPAL DISPLAY PANEL

FROM THE MAKERS OF
TYLENOL®PM

NDC 50580-843-12
Non-habit Forming

Simply
Sleep®

Diphenhydramine HCl
Nighttime Sleep Aid
Does NOT Contain Pain Reliever
*Capsule-Shaped Tablets

Actual Size

100 Caplets*